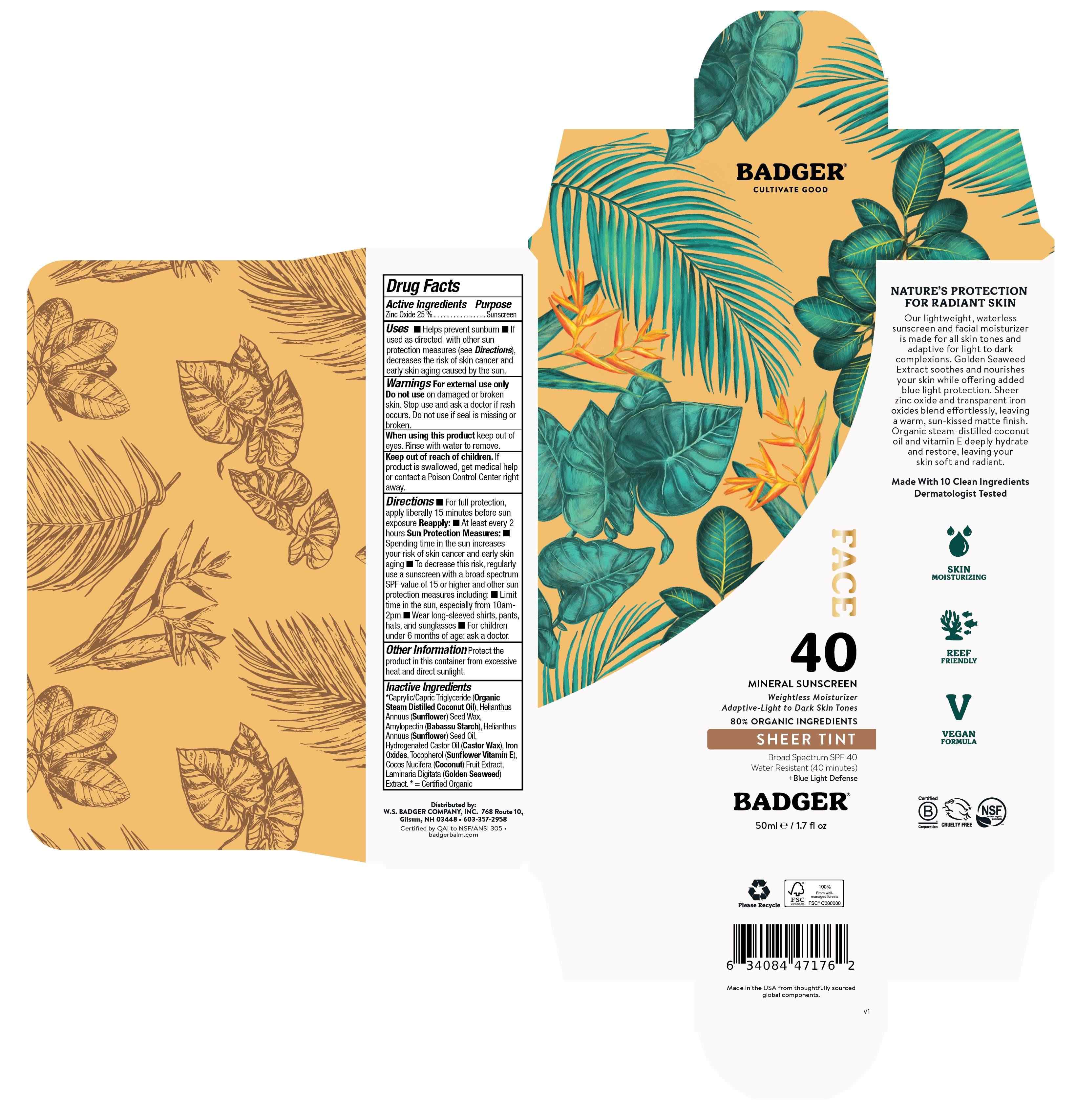 DRUG LABEL: Badger SPF 40 Tinted Mineral Face
NDC: 62206-4077 | Form: CREAM
Manufacturer: W.S. Badger Company, Inc.
Category: otc | Type: HUMAN OTC DRUG LABEL
Date: 20251217

ACTIVE INGREDIENTS: ZINC OXIDE 25 g/100 mL
INACTIVE INGREDIENTS: COCOS NUCIFERA (COCONUT) FRUIT; LAMINARIA DIGITATA; HYDROGENATED CASTOR OIL; TOCOPHEROL; CI 77499; HELIANTHUS ANNUUS (SUNFLOWER) SEED WAX; CAPRYLIC/CAPRIC TRIGLYCERIDE; AMYLOPECTIN, UNSPECIFIED SOURCE; CI 77492; CI 77491

Badger® SPF 40 Tinted Mineral Face

Drug Facts

Active Ingredient

Non-Nano Uncoated Zinc Oxide 25%

Purpose

Sunscreen

Uses

- Helps prevent sunburn
- If used as directed with other sun protection measures (see Directions), decreases the risk of skin cancer and early skin aging caused by the sun.

Warnings

For external use only

Do not use on damaged or broken skin. Stop use and ask a doctor if rash occurs. Do not use if seal is missing or broken.

When using this product keep out of eyes. Rinse with water to remove.

Keep out of reach of children. If product is swallowed, get medical help or contact a Poison Control Center right away.

Directions

- For full protection, apply liberally15 minutes before sun exposure

Reapply:

- At least every 2 hours

Sun Protection Measures:

- Spending time in the sun increases your risk of skin cancer and early skin aging
- To decrease this risk, regularly use a sunscreen with a broad spectrum SPF value of 15 or higher and other sun protection measures including:
  - Limit time in the sun, especially from 10am-2pm
  - Wear long-sleeved shirts, pants, hats, and sunglasses
- For children under 6 months of age: ask a doctor.

RECENT MAJOR CHANGES

For full protection, apply liberally15 minutes before sun exposure

Reapply:

At least every 2 hours

Sun Protection Measures:

Spending time in the sun increases your risk of skin cancer and early skin aging
To decrease this risk, regularly use a sunscreen with a broad spectrum SPF value of 15 or higher and other sun protection measures including:

Limit time in the sun, especially from 10am-2pm
Wear long-sleeved shirts, pants, hats, and sunglasses

For children under 6 months of age: ask a doctor.

Ingredients

*Caprylic/Capric Triglyceride (Organic Steam distilled Coconut Oil), Helianthus Annuus (Sunflower) Seed Wax, Amylopectin (Babassu Starsh), Helianthus Annuus (Sunflower) Seeed Oil, Hydrogenated Castor Oil (Castor Wax), Iron Oxides, Tocopherol (Sunflower Fitamin E), Cocos Nucifera (Coconut) Fruit Extract, Laminaria Digitata (Golden Seaweed) Extract. *=Certified Organic

Other Information

Protect the product in this container from excessive heat and direct sunlight.

PRINCIPAL DISPLAY PANEL - Box

Face 40 Mineral Sunscreen

Weightless Moisturizer

Adaptive-Light to Dark Skin Tones

80% ORGANIC INGREDIENTS

SHEER TINT

Broad Spectrum SPF 40

Water Resistant (40 Minutes)

+Blue Light Defense

50ml/1.7 fl oz

NATURE'S PROTECTION FOR RADIANT SKIN

Our lightweight, waterless sunscreen and facial moisturizer is made for all skin tones and adaptive for light to dark complexions. Golden Seaweed Extract soothes and nourishes your skin while offering added blue light protection. Sheer zinc oxide and transparent iron oxides blend effortlessly, leaving a warm, sun-kissed matte finish. Organic steam-distilled coconut oil and vitamin E deeply hydrate and restore, leaving your skin soft and radiant.

Made with 10 Clean Ingredients

Dermatologist Tested

SKIN MOISTURIZING

REEF FRIENDLY

Vegan Formula

Distributed by: W.S. Badger Company, Inc. 168 Route 10,

Gilsum, NH 03448 603-357-2958

Certified by QAI to NSF/ANSI 305

badgerbalm.com